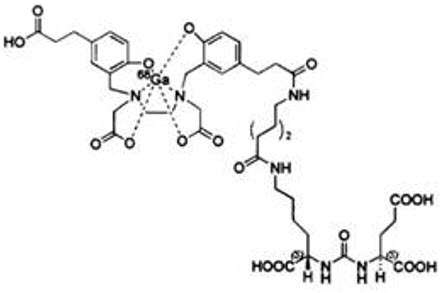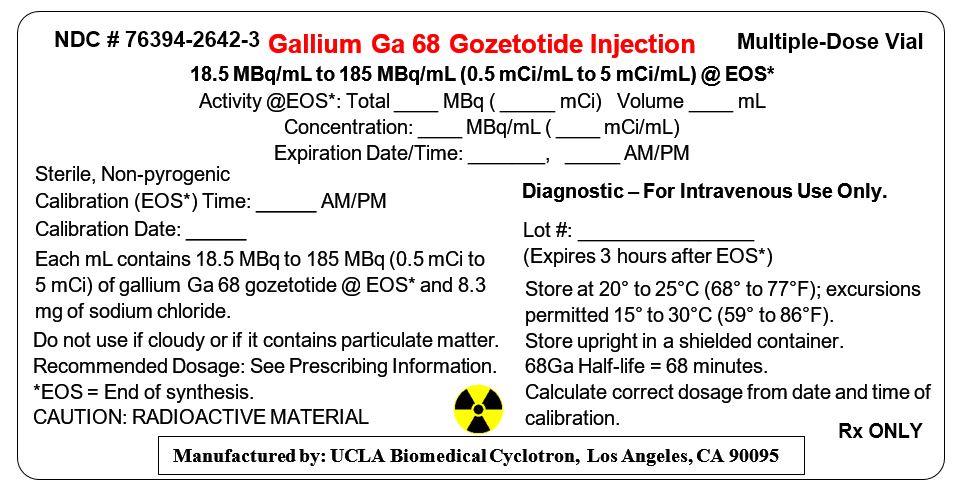 DRUG LABEL: Gallium Ga-68 PSMA-11
NDC: 76394-2642 | Form: INJECTION, SOLUTION
Manufacturer: UCLA Biomedical Cyclotron
Category: prescription | Type: HUMAN PRESCRIPTION DRUG LABEL
Date: 20250101

ACTIVE INGREDIENTS: GALLIUM GA-68 GOZETOTIDE 5 mCi/1 mL
INACTIVE INGREDIENTS: ALCOHOL; SODIUM CHLORIDE

HIGHLIGHTS OF PRESCRIBING INFORMATION

These highlights do not include all the information needed to use GALLIUM GA 68 GOZETOTIDE§ INJECTION safely and effectively. See full prescribing information for GALLIUM GA 68 GOZETOTIDE INJECTION.
GALLIUM GA 68 GOZETOTIDE INJECTION, for intravenous use
Initial U.S. Approval: 2020
(§Gozetotide is also known as PSMA-11)

1 INDICATIONS AND USAGE

Gallium Ga 68 Gozetotide Injection is a radioactive diagnostic agent indicated for positron emission tomography (PET) of prostate-specific membrane antigen (PSMA) positive lesions in men with prostate cancer:

- with suspected metastasis who are candidates for initial definitive therapy.
- with suspected recurrence based on elevated serum prostate-specific antigen (PSA) level. (1)

2 DOSAGE AND ADMINISTRATION

- Use appropriate aseptic technique and radiation safety handling measures to maintain sterility during all operations involved in the manipulation and administration of Gallium Ga 68 Gozetotide Injection. (2.1)
- The recommended adult dose is 111 MBq to 259 MBq (3 mCi to 7 mCi) as a bolus intravenous injection. (2.2)
- A diuretic expected to act within the uptake time period may be administered at the time of radiotracer injection. (2.2)
- Initiate imaging 50 to 100 minutes after administration. The patient should void immediately prior to initiation of imaging. Scan should begin caudally and proceed cranially. (2.4)
- See full prescribing information for additional preparation, administration, imaging, and radiation dosimetry information. (2)

3 DOSAGE FORMS AND STRENGTHS

Injection: clear, colorless solution in a multiple-dose vial containing 18.5 MBq/mL to 185 MBq/mL (0.5 mCi/mL to 5 mCi/mL) gallium Ga 68 gozetotide in approximately 12 mL at calibration time (3)

4 CONTRAINDICATIONS

None (4)

5 WARNINGS AND PRECAUTIONS

- Risk for misdiagnosis: Gallium Ga 68 gozetotide uptake can be seen in a variety of tumor types and in non-malignant processes. Image interpretation errors can occur with gallium Ga 68 gozetotide PET. (5.1)
- Radiation risk: Ensure safe handling to protect patients and health care workers from unintentional radiation exposure. (2.1, 5.2)

6 ADVERSE REACTIONS

The most commonly reported adverse reactions include nausea, diarrhea, and dizziness. (6)

To report SUSPECTED ADVERSE REACTIONS, contact UCLA Nuclear Medicine at 1-844-963-1855 or FDA at 1-800-FDA-1088 or www.fda.gov/medwatch.

FULL PRESCRIBING INFORMATION

1 INDICATIONS AND USAGE

Gallium Ga 68 Gozetotide Injection is indicated for positron emission tomography (PET) of prostate-specific membrane antigen (PSMA) positive lesions in men with prostate cancer:

- with suspected metastasis who are candidates for initial definitive therapy.
- with suspected recurrence based on elevated serum prostate-specific antigen (PSA) level.

2 DOSAGE AND ADMINISTRATION

2.1 Radiation Safety – Drug Handling

Handle Gallium Ga 68 Gozetotide Injection with appropriate safety measures to minimize radiation exposure [see Warnings and Precautions (5.2)] . Use waterproof gloves, effective radiation shielding, and other appropriate safety measures when preparing and handling Gallium Ga 68 Gozetotide Injection.

Radiopharmaceuticals should be used by or under the control of physicians who are qualified by specific training and experience in the safe use and handling of radionuclides, and whose experience and training have been approved by the appropriate governmental agency authorized to license the use of radionuclides.

2.2 Recommended Dosage and Administration Instructions

Recommended Dosage

In adults, the recommended amount of radioactivity to be administered for PET is 111 MBq to 259 MBq (3 mCi to 7 mCi) administered as an intravenous bolus injection.

Administration

- Use aseptic technique and radiation shielding when withdrawing and administering Gallium Ga 68 Gozetotide Injection.
- Calculate the necessary volume to administer based on calibration time and required dose.
- Inspect Gallium Ga 68 Gozetotide Injection visually for particulate matter and discoloration before administration. Do not use the drug if the solution contains particulate matter or is discolored.
- Gallium Ga 68 Gozetotide Injection may be diluted with sterile 0.9% Sodium Chloride Injection, USP.
- Assay the final dose immediately before administration to the patient in a dose calibrator.
- After injection of Gallium Ga 68 Gozetotide Injection, administer an intravenous flush of sterile 0.9% Sodium Chloride Injection, USP to ensure full delivery of the dose.
- Dispose of any unused drug in a safe manner in compliance with applicable regulations.
- Unless contraindicated, a diuretic expected to act within the uptake time period may be administered at the time of radiotracer injection to potentially decrease artifact from radiotracer accumulation in the urinary bladder and ureters.

2.3 Patient Preparation Prior to PET Imaging

Instruct patients to drink a sufficient amount of water to ensure adequate hydration prior to administration of Gallium Ga 68 Gozetotide Injection and to continue to drink and void frequently following administration to reduce radiation exposure, particularly during the first hour after administration [see Warnings and Precautions (5.2)] .

2.4 Image Acquisition

Position the patient supine with arms above the head. Begin PET scanning 50 to 100 minutes after the intravenous administration of Gallium Ga 68 Gozetotide Injection. Patients should void immediately prior to image acquisition and that image acquisition should begin at the proximal thighs and proceed cranially to the skull base or skull vertex. Adapt imaging technique according to the equipment used and patient characteristics in order to obtain the best image quality possible.

2.5 Image Interpretation

Gallium Ga 68 Gozetotide binds to prostate-specific membrane antigen (PSMA). Based on the intensity of the signals, PET images obtained using Gallium Ga 68 Gozetotide Injection indicate the presence of PSMA in tissues. Lesions should be considered suspicious if uptake is greater than physiologic uptake in that tissue or greater than adjacent background if no physiologic uptake is expected. Tumors that do not bear PSMA will not be visualized. Increased uptake in tumors is not specific for prostate cancer [see Warnings and Precautions (5.1)] .

2.6 Radiation Dosimetry

Estimated radiation absorbed doses per injected activity for organs and tissues of adult male patients following an intravenous bolus of Gallium Ga 68 Gozetotide Injection are shown in Table 1.

The effective radiation dose resulting from the administration of 259 MBq (7 mCi) is about 4.4 mSv. The radiation doses for this administered dose to the critical organs, which are the kidneys, urinary bladder, and spleen, are 96.2 mGy, 25.4 mGy, and 16.8 mGy, respectively.

These radiation doses are for Gallium Ga 68 Gozetotide Injection alone. If CT or a transmission source are used for attenuation correction, the radiation dose will increase by an amount that varies by technique.

Table 1: Estimated Radiation Absorbed Dose per Injected Activity in Selected Organs and Tissues of Adults after Intravenous Administration of Gallium Ga 68 Gozetotide Injection
Organ | Absorbed dose (mGy/MBq)
Organ | Mean | SD
Adrenals | 0.0156 | 0.0014
Brain | 0.0104 | 0.0011
Breasts | 0.0103 | 0.0011
Gallbladder | 0.0157 | 0.0012
Lower Colon | 0.0134 | 0.0009
Small Intestine | 0.0140 | 0.0020
Stomach | 0.0129 | 0.0008
Heart | 0.0120 | 0.0009
Kidneys | 0.3714 | 0.0922
Liver | 0.0409 | 0.0076
Lungs | 0.0111 | 0.0007
Muscle | 0.0103 | 0.0003
Pancreas | 0.0147 | 0.0009
Red Marrow | 0.0114 | 0.0016
Skin | 0.0091 | 0.0003
Spleen | 0.0650 | 0.0180
Testes | 0.0111 | 0.0006
Thymus | 0.0105 | 0.0006
Thyroid | 0.0104 | 0.0006
Urinary Bladder | 0.0982 | 0.0286
Total Body | 0.0143 | 0.0013
Effective Dose (mSv/MBq) | 0.0169 | 0.0015

3 DOSAGE FORMS AND STRENGTHS

Injection: supplied as a clear, colorless solution in a multiple-dose vial containing 18.5 MBq/mL to 185 MBq/mL (0.5 mCi/mL to 5 mCi/mL) of gallium Ga 68 gozetotide in approximately 12 mL at calibration time.

4 CONTRAINDICATIONS

None

5 WARNINGS AND PRECAUTIONS

5.1 Risk for Misdiagnosis

Image interpretation errors can occur with gallium Ga 68 gozetotide PET. A negative image does not rule out the presence of prostate cancer and a positive image does not confirm the presence of prostate cancer. The performance of Gallium Ga 68 Gozetotide Injection for imaging of biochemically recurrent prostate cancer seems to be affected by serum PSA levels and by site of disease [See Clinical Studies (14)] . The performance of Gallium Ga 68 Gozetotide Injection for imaging of metastatic pelvic lymph nodes prior to initial definitive therapy seems to be affected by Gleason score [See Clinical Studies (14)] . Gallium Ga 68 gozetotide uptake is not specific for prostate cancer and may occur with other types of cancer as well as non-malignant processes such as Paget's disease, fibrous dysplasia, and osteophytosis. Clinical correlation, which may include histopathological evaluation of the suspected prostate cancer site, is recommended.

5.2 Radiation Risks

Gallium Ga 68 Gozetotide Injection contributes to a patient's overall long-term cumulative radiation exposure. Long-term cumulative radiation exposure is associated with an increased risk for cancer. Ensure safe handling to minimize radiation exposure to the patient and health care workers. Advise patients to hydrate before and after administration and to void frequently after administration [see Dosage and Administration (2.1, 2.3)] .

6 ADVERSE REACTIONS

Clinical Trials Experience

Because clinical trials are conducted under widely varying conditions, adverse reaction rates observed in the clinical trials of a drug cannot be directly compared to rates in the clinical trials of another drug and may not reflect the rates observed in practice.

The safety of Gallium Ga 68 Gozetotide Injection was evaluated in 960 patients, each receiving one dose of Gallium Ga 68 Gozetotide Injection. The average injected activity was 188.7 ± 40.7 MBq (5.1 ± 1.1 mCi).

The most commonly reported adverse reactions were nausea, diarrhea, and dizziness, occurring at a rate of < 1%.

7 DRUG INTERACTIONS

Androgen deprivation therapy and other therapies targeting the androgen pathway

Androgen deprivation therapy (ADT) and other therapies targeting the androgen pathway, such as androgen receptor antagonists, can result in changes in uptake of gallium Ga 68 gozetotide in prostate cancer. The effect of these therapies on performance of gallium Ga 68 gozetotide PET has not been established.

8 USE IN SPECIFIC POPULATIONS

8.1 Pregnancy

Risk Summary

Gallium Ga 68 Gozetotide Injection is not indicated for use in females. There are no available data with Gallium Ga 68 Gozetotide Injection use in pregnant women to evaluate for a drug-associated risk of major birth defects, miscarriage, or adverse maternal or fetal outcomes. All radiopharmaceuticals, including Gallium Ga 68 Gozetotide Injection, have the potential to cause fetal harm depending on the fetal stage of development and the magnitude of the radiation dose. Animal reproduction studies have not been conducted with gallium Ga 68 gozetotide.

8.2 Lactation

Risk Summary

Gallium Ga 68 Gozetotide Injection is not indicated for use in females. There are no data on the presence of gallium Ga 68 gozetotide in human milk, the effect on the breastfed infant, or the effect on milk production.

8.4 Pediatric Use

The safety and effectiveness of Gallium Ga 68 Gozetotide Injection have not been established in pediatric patients.

8.5 Geriatric Use

The efficacy of Gallium Ga 68 Gozetotide Injection in geriatric patients with prostate cancer is based on data from two prospective studies [see Clinical Studies (14)] . Of the total number of subjects in these studies of Gallium Ga 68 Gozetotide Injection, 691 of 960 (72%) were 65 years of age and older (72%), While 195 (20%) were 75 years of age and older.

The efficacy and safety profiles of Gallium Ga 68 Gozetotide Injection appear similar in younger adult and geriatric patients with prostate cancer, although the number of younger adult patients in the trials was not large enough to allow definitive comparison.

10 OVERDOSAGE

In the event of an overdose of Gallium Ga 68 Gozetotide Injection, reduce the radiation absorbed dose to the patient where possible by increasing the elimination of the drug from the body using hydration and frequent bladder voiding. A diuretic might also be considered. If possible, an estimate of the radiation effective dose given to the patient should be made.

11 DESCRIPTION

11.1 Chemical Characteristics

Gallium Ga 68 Gozetotide Injection is a radioactive diagnostic agent for intravenous administration. It contains 5 mcg gozetotide, 18.5 MBq/mL to 185 MBq/mL (0.5 mCi/mL to 5 mCi/mL) of gallium Ga 68 gozetotide at calibration time, 1 mL ethanol, 1 mL water for injection, and 10 mL of 0.9% sodium chloride solution (approximately 12 mL total volume). Gallium Ga 68 Gozetotide Injection is provided as a sterile, pyrogen free, clear, colorless solution for intravenous use, with a pH between 4.0 and 7.0. Gozetotide is also known as PSMA-11.

Gallium Ga 68 gozetotide is a urea based peptidomimetic that has a covalently bound chelator (HBED-CC). The peptide has the amino acid sequence Glu-NH-CO-NH-Lys(Ahx)-HBED-CC. Gallium Ga 68 gozetotide has a molecular weight of 1011.91 g/mol and its chemical structure is shown in Figure 1.

Figure 1: Chemical Structure of Gallium Ga 68 Gozetotide

11.2 Physical Characteristics

Gallium-68 (Ga 68) decays with a half-life of 68 minutes to stable zinc-68. Table 2 and Table 3 display the principal radiation emission data and physical decay of Ga 68.

Table 2: Principal Radiation Emission Data (>1%) for Gallium Ga 68
Radiation/ Emission | % Disintegration | Mean Energy (MeV)
beta+ | 88% | 0.8360
beta+ | 1.1% | 0.3526
gamma | 178% | 0.5110
gamma | 3.0% | 1.0770
X-ray | 2.8% | 0.0086
X-ray | 1.4% | 0.0086

Table 3: Physical Decay Chart for Gallium Ga 68
Minutes | Fraction Remaining
0 | 1
15 | 0.858
30 | 0.736
60 | 0.541
90 | 0.398
120 | 0.293
180 | 0.158
240 | 0.086
360 | 0.025

11.3 External Radiation

Table 4 displays the radiation attenuation by lead shielding of Ga 68.

Table 4: Radiation Attenuation of 511 keV Photons by Lead (Pb) Shielding
Shield Thickness (Pb) mm | Coefficient of Attenuation
6 | 0.5
12 | 0.25
17 | 0.1
34 | 0.01
51 | 0.001

12 CLINICAL PHARMACOLOGY

12.1 Mechanism of Action

Gallium Ga 68 gozetotide binds to prostate-specific membrane antigen (PSMA). It binds to cells that express PSMA, including malignant prostate cancer cells, which usually overexpress PSMA. Gallium-68 (Ga 68) is a β+ emitting radionuclide that allows positron emission tomography (PET).

12.2 Pharmacodynamics

The relationship between gallium Ga 68 gozetotide plasma concentrations and successful imaging was not explored in clinical trials.

12.3 Pharmacokinetics

Distribution

Intravenously injected gallium Ga 68 gozetotide is cleared from the blood and is accumulated preferentially in the liver (15%), kidneys (7%), spleen (2%), and salivary glands (0.5%). Gallium Ga 68 gozetotide uptake is also seen in the adrenals and prostate. There is no uptake in the cerebral cortex or in the heart, and usually lung uptake is low.

Elimination

A total of 14% of the injected dose is excreted in urine in the first 2 hours post-injection.

13 NONCLINICAL TOXICOLOGY

13.1 Carcinogenesis, Mutagenesis, Impairment of Fertility

No long-term animal studies were performed to evaluate the carcinogenicity potential of gallium Ga 68 gozetotide.

14 CLINICAL STUDIES

The safety and efficacy of Gallium Ga 68 Gozetotide Injection were established in two prospective, open-label studies, PSMA-PreRP (NCT03368547 and NCT02919111) and PSMA-BCR (NCT02940262 and NCT02918357) in men with prostate cancer.

PSMA-PreRP

This two-center study enrolled 325 patients with biopsy-proven prostate cancer who were considered candidates for prostatectomy and pelvic lymph node dissection. All enrolled patients met at least one of the following criteria: serum prostate-specific antigen (PSA) of at least 10 ng/mL, tumor stage cT2b or greater, or Gleason score greater than 6. Each patient received a single gallium Ga 68 gozetotide PET/CT or PET/MR from mid-thigh to skull base.

A total of 123 patients (38%) proceeded to standard-of-care prostatectomy and template pelvic lymph node dissection and had sufficient histopathology data for evaluation (evaluable patients). Three members of a pool of six central readers independently interpreted each PET scan for the presence of abnormal gallium Ga 68 gozetotide uptake in pelvic lymph nodes located in the common iliac, external iliac, internal iliac, and obturator subregions bilaterally as well as in any other pelvic location. The readers were blinded to all clinical information except for the history of prostate cancer prior to definitive treatment. Extrapelvic sites and the prostate gland itself were not analyzed in this study. For each patient, gallium Ga 68 gozetotide PET results and reference standard histopathology obtained from dissected pelvic lymph nodes were compared by region (left hemipelvis, right hemipelvis, and other).

For the 123 evaluable patients, the mean age was 65 years (range 45 to 76 years), and 89% were white. The median serum PSA was 11.8 ng/mL. The summed Gleason score was 7 for 44%, 8 for 20%, and 9 for 31% of the patients, with the remainder of the patients having Gleason scores of 6 or 10.

Table 5 compares majority PET reads to pelvic lymph node histopathology results at the patient-level with region matching, such that at least one true positive region defines a true positive patient. As shown, approximately 24% of subjects studied were found to have pelvic nodal metastases based on histopathology (95% confidence interval: 17%, 32%).

Table 5: Patient-Level Performance of Gallium Ga 68 Gozetotide PET for Detection of Pelvic Lymph Node Metastasis [with region matching where at least one true positive region defines a true positive patient] in the PSMA-PreRP Study (n=123)
 |  | Histopathology |  | Predictive value [PPV: positive predictive value, NPV: negative predictive value] (95% CI)
 |  | Positive | Negative | Predictive value [PPV: positive predictive value, NPV: negative predictive value] (95% CI)
PET scan | Positive | 14 | 9 | PPV 61% (41%, 81%)
PET scan | Negative | 16 | 84 | NPV 84% (79%, 91%)
Total |  | 30 | 93
Diagnostic performance (95% CI) |  | Sensitivity 47% (29%, 65%) | Specificity 90% (84%, 96%)

Among the pool of six readers, sensitivity ranged from 36% to 60%, specificity from 83% to 96%, positive predictive value from 38% to 80%, and negative predictive value from 80% to 88%.

In an exploratory subgroup analysis based on summed Gleason score, there was a numerical trend toward more true positives in patients with Gleason score of 8 or higher compared to those with Gleason score of 7 or lower.

An exploratory analysis was performed to estimate the sensitivity and specificity for pelvic nodal metastasis detection in all scanned patients, including the patients who were lacking histopathology reference standard. An imputation method was used based on patient-specific factors. This exploratory analysis resulted in an imputed sensitivity of 47%, with a 95% confidence interval ranging from 38% to 55%, and an imputed specificity of 74%, with a 95% confidence interval ranging from 68% to 80% for all patients imaged with gallium Ga 68 gozetotide PET.

PSMA-BCR

This two-center study enrolled 635 patients with biochemical evidence of recurrent prostate cancer after definitive therapy, defined by serum PSA of >0.2 ng/mL more than 6 weeks after prostatectomy or by an increase in serum PSA of at least 2 ng/mL above nadir after definitive radiotherapy. All patients received a single gallium Ga 68 gozetotide PET/CT or PET/MR from mid-thigh to skull base. Three members of a pool of nine independent central readers evaluated each scan for the presence and regional location (20 subregions grouped into four regions) of abnormal gallium Ga 68 gozetotide uptake suggestive of recurrent prostate cancer. The readers were blinded to all clinical information other than type of primary therapy and most recent serum PSA level.

A total of 469 patients (74%) had at least one positive region detected by gallium Ga 68 gozetotide PET majority read. The distribution of gallium Ga 68 gozetotide PET positive regions was 34% bone, 25% prostate bed, 25% pelvic lymph node, and 17% extrapelvic soft tissue. Two hundred and ten patients had composite reference standard information collected in a PET positive region (evaluable patients), consisting of at least one of the following: histopathology, imaging (bone scintigraphy, CT, or MRI) acquired at baseline or within 12 months after gallium Ga 68 gozetotide PET, or serial serum PSA. Composite reference standard information for gallium Ga 68 gozetotide PET negative regions was not systematically collected in this study.

In the 210 evaluable patients, the mean age was 70 years (range 49 to 88 years) and 82% were 65 years of age or older. White patients made up 90% of the group. The median serum PSA was 3.6 ng/mL. Prior treatment included radical prostatectomy in 64% and radiotherapy in 73%.

Of the 210 evaluable patients, 192 patients (91%) were found to be true positive in one or more regions against the composite reference standard (95% confidence interval: 88%, 95%). Among the pool of nine readers used in the study, the proportion of patients who were true positive in one or more regions ranged from 82% to 97%. The prostate bed had the lowest proportion of true positive results at the region-level (76% versus 96% for non-prostate regions).

An exploratory analysis was also performed in which gallium Ga 68 gozetotide PET positive patients who lacked reference standard information were imputed using an estimated likelihood that at least one location-matched PET positive lesion was reference standard positive based on patient-specific factors. In this exploratory analysis, 340 of 475 patients (72%) were imputed as true positive in one or more regions (95% confidence interval: 68%, 76%).

In another exploratory analysis using the same imputation approach for PET positive patients who lacked reference standard information, 340 of 635 patients (54%) were correctly detected as true positive (95% confidence interval: 50%, 57%) among all BCR patients who received a PET scan, whether it was read as positive or negative.

The likelihood of identifying a gallium Ga 68 gozetotide PET positive lesion in this study generally increased with higher serum PSA level. Table 6 shows the patient-level gallium Ga 68 gozetotide PET results stratified by serum PSA level. The mean time between PSA measurement and PET scan was 40 days with a range of 0 to 367 days. Percent PET positivity was calculated as the proportion of patients with a positive gallium Ga 68 gozetotide PET out of all patients scanned. Percent PET positivity includes patients determined to be either true positive or false positive as well as those in whom such determination was not made due to the absence of composite reference standard data.

Table 6: Patient-Level Gallium Ga 68 Gozetotide PET Results and Percent PET Positivity Stratified by Serum PSA Level in the PSMA-BCR Study (n=628) [7 patients were excluded from this table due to protocol deviations]
PSA (ng/mL) | PET positive patients |  |  |  | PET negative patients | Percent PET positivity [Percent PET positivity = PET positive patients/total patients scanned] (95% CI)
PSA (ng/mL) | Total | TP [TP: true positive, FP: false positive] | FP | Without reference standard | PET negative patients | Percent PET positivity [Percent PET positivity = PET positive patients/total patients scanned] (95% CI)
PSA (ng/mL) | Total | With reference standard |  | Without reference standard | PET negative patients | Percent PET positivity [Percent PET positivity = PET positive patients/total patients scanned] (95% CI)
<0.5 | 48 | 11 | 1 | 36 | 87 | 36% (27%, 44%)
<0.5 | 48 | 12 |  | 36 | 87 | 36% (27%, 44%)
0.5 and <1 | 44 | 15 | 3 | 26 | 35 | 56% (45%, 67%)
0.5 and <1 | 44 | 18 |  | 26 | 35 | 56% (45%, 67%)
1 and <2 | 71 | 29 | 1 | 41 | 15 | 83% (75%, 91%)
1 and <2 | 71 | 30 |  | 41 | 15 | 83% (75%, 91%)
2 | 299 | 137 | 13 | 149 | 29 | 91% (88%, 94%)
2 | 299 | 150 |  | 149 | 29 | 91% (88%, 94%)
Total | 462 | 192 | 18 | 252 | 166 | 74% (70%, 77%)
Total | 462 | 210 |  | 252 | 166 | 74% (70%, 77%)

16 HOW SUPPLIED/STORAGE AND HANDLING

How Supplied

Gallium Ga 68 Gozetotide Injection (NDC 76394-2642-3) is a clear, colorless solution, supplied in a capped glass vial containing 18.5 MBq/mL to 185 MBq/mL (0.5 mCi/mL to 5 mCi/mL) of gallium 68 gozetotide at calibration time, in approximately 12 mL. The contents of each vial are sterile, pyrogen-free and preservative-free. The expiration date and time are provided on the container label. Use Gallium Ga 68 Gozetotide Injection within 3 hours of calibration time.

STORAGE AND HANDLING

Storage and Handling

Store Gallium Ga 68 Gozetotide Injection upright in a lead shielded container at 25°C (77°F); excursions are permitted from 15°C to 30°C (59°F to 86°F). Store Gallium Ga 68 Gozetotide Injection within the original container in radiation shielding.

Receipt, transfer, handling, possession, or use of this product is subject to the radioactive material regulations and licensing requirements of the U.S. Nuclear Regulatory Commission, Agreement States, or Licensing States as appropriate.

17 PATIENT COUNSELING INFORMATION

Adequate Hydration

Instruct patients to drink a sufficient amount of water to ensure adequate hydration before their PET study and urge them to drink and urinate as often as possible during the first hours following the administration of Gallium Ga 68 Gozetotide Injection, in order to reduce radiation exposure [see Dosage and Administration (2.3) and Warnings and Precautions (5.2)] .

Manufactured and Distributed by:
University of California, Los Angeles
UCLA Biomedical Cyclotron Facility
780 Westwood Plaza
Los Angeles, CA 90095
(310) 794-7638

PRINCIPAL DISPLAY PANEL - 12 mL Vial Label

NDC # 76394-2642-3
Gallium Ga 68 Gozetotide Injection
Multiple-Dose Vial

18.5 MBq/mL to 185 MBq/mL (0.5 mCi/mL to 5 mCi/mL) @ EOS*
Activity @EOS*: Total ____ MBq (_____ mCi) Volume ____ mL
Concentration: ____ MBq/mL (____ mCi/mL)
Expiration Date/Time: _______, _____ AM/PM

Sterile, Non-pyrogenic
Calibration (EOS*) Time: _____ AM/PM
Calibration Date: _____

Each mL contains 18.5 MBq to 185 MBq (0.5 mCi to
5 mCi) of gallium Ga 68 gozetotide @ EOS* and 8.3 mg of
sodium chloride.

Do not use if cloudy or if it contains particulate matter.
Recommended Dosage: See Prescribing Information.
*EOS = End of synthesis.
CAUTION: RADIOACTIVE MATERIAL

Diagnostic – For Intravenous Use Only.

Lot #: ________________
(Expires 3 hours after EOS*)

Store at 20° to 25°C (68° to 77°F);
excursions permitted to 15° to 30°C (59° to 86°F).
Store upright in a shielded container.
68Ga Half-life = 68 minutes.
Calculate correct dosage from date and time of
calibration.

Rx ONLY

Manufactured by: UCLA Biomedical Cyclotron, Los Angeles, CA 90095